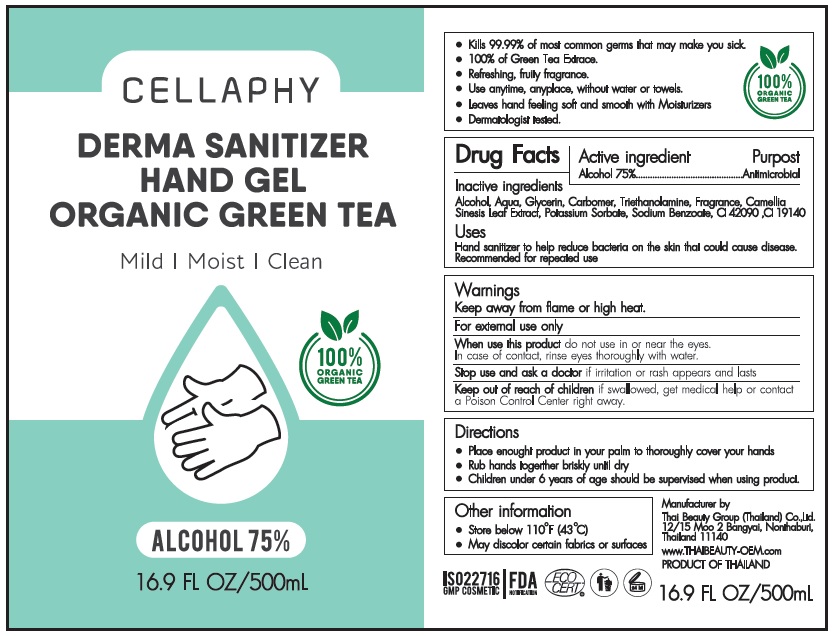 DRUG LABEL: CELLAPHY DERMA SANITIZER HAND Gel
NDC: 79946-101 | Form: GEL
Manufacturer: THAI BEAUTY GROUP (THAILAND) COMPANY LIMITED
Category: otc | Type: HUMAN OTC DRUG LABEL
Date: 20200814

ACTIVE INGREDIENTS: ALCOHOL 75 mL/100 mL
INACTIVE INGREDIENTS: WATER; GLYCERIN; CARBOMER HOMOPOLYMER, UNSPECIFIED TYPE; TROLAMINE; GREEN TEA LEAF; POTASSIUM SORBATE; SODIUM BENZOATE; FD&C BLUE NO. 1; FD&C YELLOW NO. 5

CELLAPHY DERMA SANITIZER HAND GEL

Active ingredient

Alcohol 75%

Purpose

Antimicrobial

Inactive ingredients

Alcohol, Aqua, Glycerin, Carbomer, Triethnolamine, Fragrance, Camellia Sinensis Leaf Extract, Potassium Sorbate, Sodium Benzoate, CI 42090, CI 19140

Uses

Hand sanitizer to help reduce bacteria on the skin that could cause disease. Recommended for repeated use

Warnings:

Keep away from fire or high heat.

For external use only.

When use this product do not use in or near the eyes. In case of contact, rinse eyes thoroughly with water.

Stop use and ask a doctor if irritation or rash appears and lasts

Keep out of reach of children. If swallowed, get medical help or contact a Poison Control Center right away.

Directions

- Place enough product in your palm to thoroughly cover your hands
- Rub hands together briskly until dry
- Children under 6 years of age should be supervised when using product.

Other information

- Store below 110°F(43°C)
- May discolor certain fabrics or surfaces

ORGANIC GREEN TEA

Mild | Moist | Clean

100% ORGANIC GREEN TEA

- Kills 99.99% of most common germs that may make you sick.
- 100% of Green Tea Extract.
- Refreshing, fruity fragrance.
- Use anytime, anyplace, without water or towels.
- Leaves hand feeling soft and smooth with Moisturizers
- Dermatologist tested.

Manufacturer by

Thai Beauty Group (Thailand) Co., Ltd.
12/15 Moo 2 Bangyal, Nanthaburi,
Thailand 11140

www.THAIBEAUTY-OEM.com

PRODUCT OF THAILAND